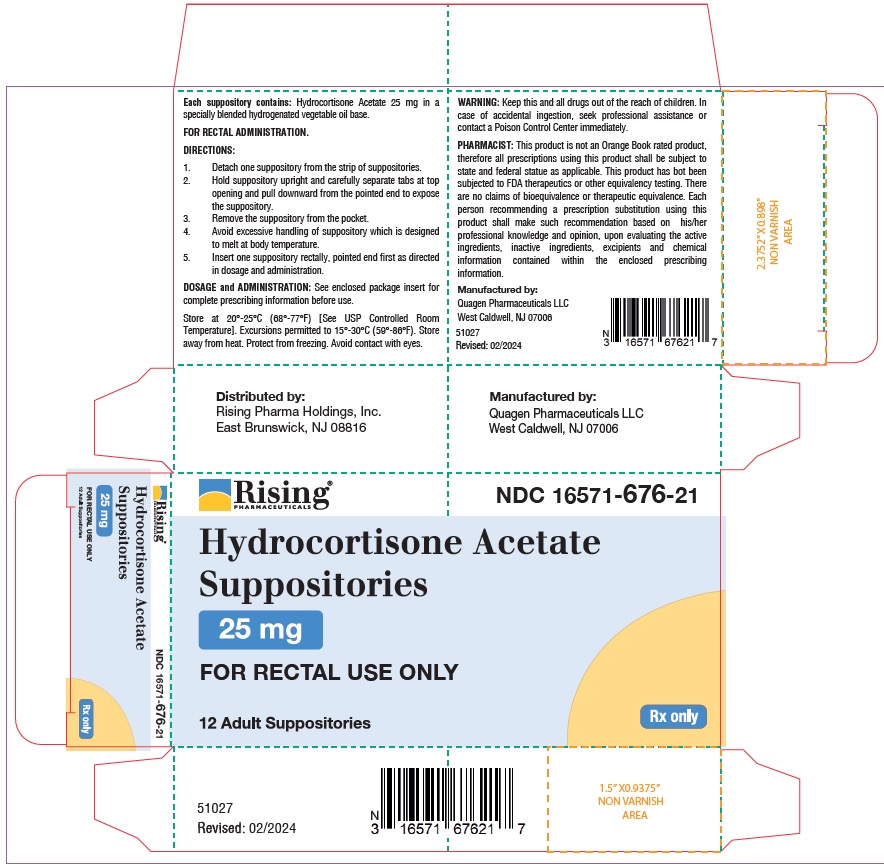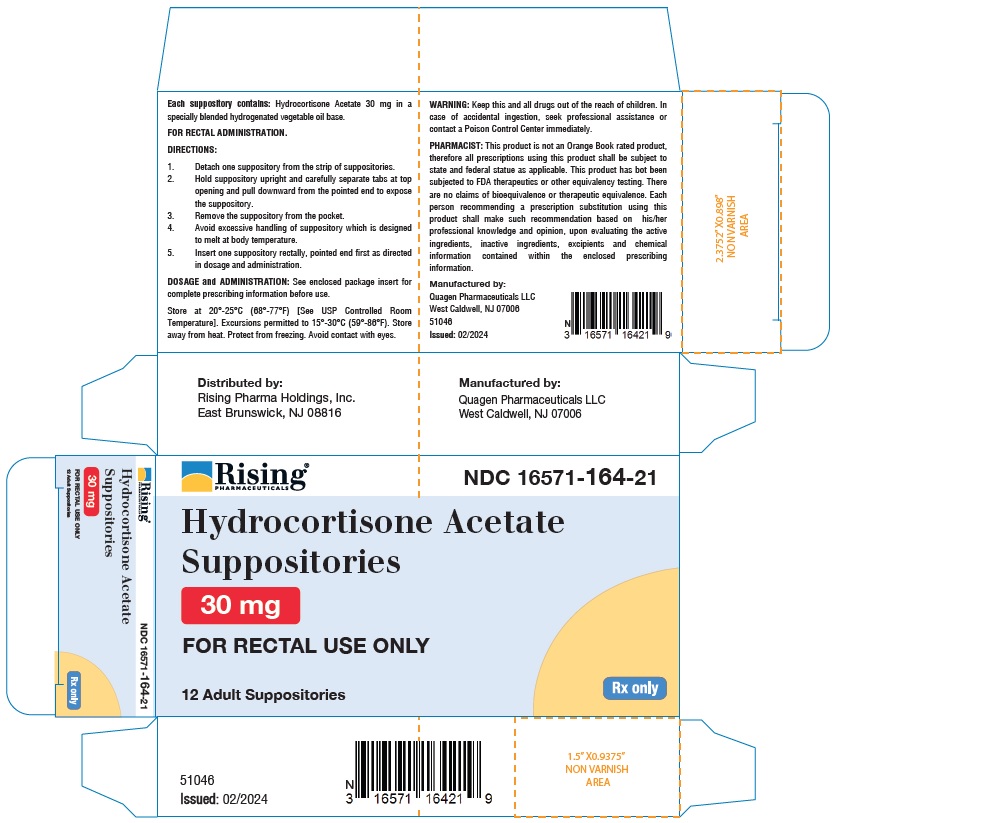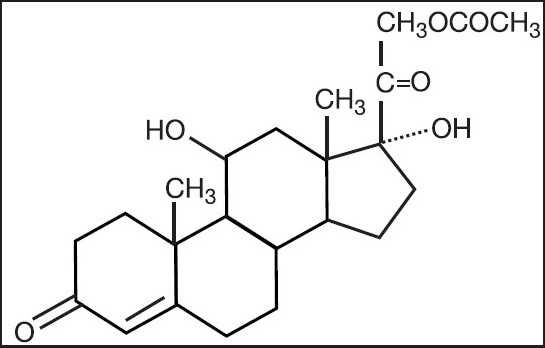 DRUG LABEL: Hydrocortisone Acetate
NDC: 16571-676 | Form: SUPPOSITORY
Manufacturer: Rising Pharma Holdings, Inc.
Category: prescription | Type: Human Prescription Drug Label
Date: 20240220

ACTIVE INGREDIENTS: HYDROCORTISONE ACETATE 25 mg/1 1
INACTIVE INGREDIENTS: HYDROGENATED PALM KERNEL OIL

Hydrocortisone Acetate Suppositories, 25 mg
Hydrocortisone Acetate Suppositories, 30 mg
For Rectal Administration
Rx only

DESCRIPTION

Each Hydrocortisone Acetate Suppository for rectal administration contains 25 mg hydrocortisone acetate, USP in a specially blended hydrogenated vegetable oil base.

Each Hydrocortisone Acetate Suppository for rectal administration contains 30 mg hydrocortisone acetate, USP in a specially blended hydrogenated vegetable oil base.

Hydrocortisone acetate is a corticosteroid. The molecular weight of hydrocortisone acetate is 404.50.

Chemically, hydrocortisone acetate is pregn-4-ene-3, 20 dione, 21-(acetyloxy)-11, 17-dihydroxy-, (11ß)- with an empirical formula of C H O and the following structural formula:

CLINICAL PHARMACOLOGY

In normal subjects, about 26% of hydrocortisone acetate is absorbed when the hydrocortisone acetate suppository is applied to the rectum. Absorption of hydrocortisone acetate may vary across abraded or inflamed surfaces.

Topical steroids are primarily effective because of their anti-inflammatory, anti-pruritic and vasoconstrictive action.

INDICATIONS AND USAGE

Hydrocortisone acetate suppositories are indicated for use in inflamed hemorrhoids, post-irradiation (factitial) proctitis, as an adjunct in the treatment of chronic ulcerative colitis, cryptitis, other inflammatory conditions of anorectum, and pruritus ani.

CONTRAINDICATIONS

Hydrocortisone acetate suppositories are contraindicated in those patients having a history of hypersensitivity to hydrocortisone acetate or any of the components.

PRECAUTIONS

Do not use hydrocortisone acetate suppositories unless adequate proctologic examination is made.
If irritation develops, the product should be discontinued and appropriate therapy instituted.
In the presence of an infection, the use of an appropriate antifungal or antibacterial agent should be instituted. If a favorable response does not occur promptly, hydrocortisone acetate should be discontinued until the infection has been adequately controlled.

Carcinogenesis

No long-term studies in animals have been performed to evaluate the carcinogenic potential of corticosteroid suppositories.

PREGNANCY CATEGORY C

In laboratory animals, topical steroids have been associated with an increase in the incidence of fetal abnormalities when gestating females have been exposed to rather low dosage levels. There are no adequate and well-controlled studies in pregnant women.
Hydrocortisone acetate suppositories should only be used during pregnancy if the potential benefit justifies the risk of the fetus. Drugs of this class should not be used extensively on pregnant patients, in large amounts, or for prolonged periods of time.
It is not known whether this drug is excreted in human milk, and because many drugs are excreted in human milk and because of the potential for serious adverse reactions in nursing infants from hydrocortisone acetate suppositories, a decision should be made whether to discontinue nursing or to discontinue the drug, taking into account the importance of the drug to the mother.

ADVERSE REACTIONS

The following local adverse reactions have been reported with hydrocortisone acetate suppositories; burning, itching, irritation, dryness, folliculitis, hypopigmentation, allergic contact dermatitis, secondary infection.
To report SUSPECTED ADVERSE REACTIONS, contact Rising Pharma Holdings, Inc. at 1-844-874-7464, or FDA at 1-800-FDA-1088 or www.fda.gov/medwatch.

Drug abuse and dependence have not been reported in patients treated with hydrocortisone acetate suppositories.

OVERDOSAGE

If signs and symptoms of systemic overdosage occur, discontinue use.

DOSAGE AND ADMINISTRATION

Usual dosage: One suppository in the rectum twice daily morning and night for two weeks, in nonspecific proctitis. In more severe cases, one suppository three times daily; or two suppositories twice daily. In factitial proctitis, recommended therapy is six to eight weeks or less, according to response.

HOW SUPPLIED

Hydrocortisone acetate suppositories 25 mg are off-white, smooth surfaced and bullet shaped with one pointed end.
Box of 12 suppositories, NDC 16571-676-21
Box of 24 suppositories, NDC 16571-676-42

Hydrocortisone acetate suppositories 30 mg are off-white, smooth surfaced and bullet shaped with one pointed end.
Box of 12 suppositories, NDC 16571-164-21

STORAGE

Store at 20°-25°C (68°-77°F) [See USP Controlled Room Temperature]. Excursions permitted to 15°-30°C (59°-86°F). Store away from heat. Protect from freezing. Avoid contact
with eyes.
KEEP THIS AND ALL DRUGS OUT OF THE REACH OF CHILDREN. In case of accidental ingestion, seek professional assistance or contact a Poison Control Center immediately.

PHARMACIST
This product is not an Orange Book rated product, therefore all prescriptions using this product shall be subject to state and federal statutes as applicable. This product has not been subjected to FDA therapeutic or other equivalency testing. There are no claims of bioequivalence or therapeutic equivalence. Each person recommending a prescription substitution using this product shall make such recommendation based on his/her professional knowledge and opinion, upon evaluating the active ingredients, inactive ingredients, excipients and chemical information contained within the enclosed prescribing information.
Rx Only
Distributed by:
Rising Pharma Holdings, Inc.
East Brunswick, NJ 08816
Manufactured by:
Quagen Pharmaceuticals LLC
West Caldwell, NJ 07006
52030/52050
Revised: 02/2024

PACKAGE LABEL.PRINCIPAL DISPLAY PANEL

Rising® NDC 16571-676-21
Hydrocortisone Acetate Suppositories
25 mg
For Rectal Administration
12 Adult Suppositories Rx only

Rising® NDC 16571-164-21

Hydrocortisone Acetate Suppositories
30 mg
For Rectal Administration
12 Adult Suppositories Rx only